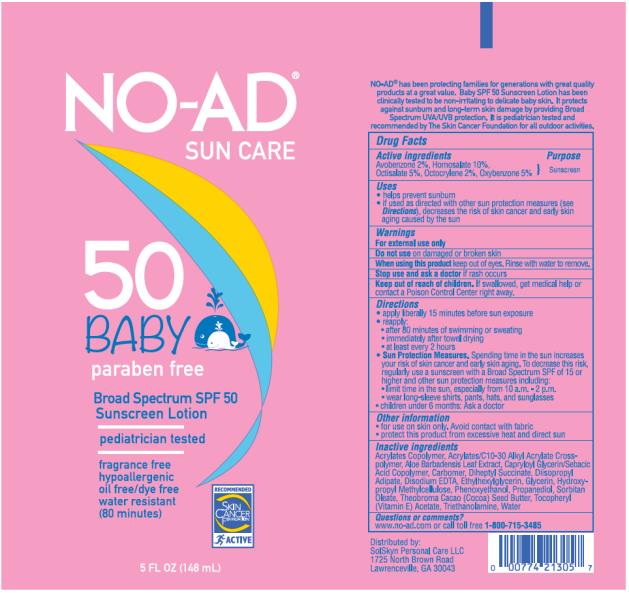 DRUG LABEL: NO-AD SunCare Ltn SPF 50
NDC: 70281-134 | Form: LOTION
Manufacturer: SolSkyn Personal Care LLC
Category: otc | Type: HUMAN OTC DRUG LABEL
Date: 20180215

ACTIVE INGREDIENTS: AVOBENZONE 2 g/100 g; HOMOSALATE 10 g/100 g; OCTISALATE 5 g/100 g; OCTOCRYLENE 2 g/100 g; OXYBENZONE 5 g/100 g
INACTIVE INGREDIENTS: CARBOMER INTERPOLYMER TYPE A (55000 CPS); ALOE VERA LEAF; CARBOXYPOLYMETHYLENE; DIHEPTYL SUCCINATE; DIISOPROPYL ADIPATE; DISODIUM EDTA-COPPER; ETHYLHEXYLGLYCERIN; GLYCERIN; HYPROMELLOSES; PHENOXYETHANOL; PROPANEDIOL; SORBITAN MONOOLEATE; COCOA BUTTER; ALPHA-TOCOPHEROL ACETATE; TROLAMINE; WATER

NO-AD Baby SPF 50 Ltn 5oz

NO-AD Sun Care Baby Broad Spectrum SPF 50 Sunscreen Lotion

Active Ingredients

Avobenzone 2%, Homosalate 10%, Octisalate 5%,Octocrylene 2%, Oxybenzone 5%

Purpose

Sunscreen

Uses

- helps prevent sunburn
- if used as directed with other sun protection measures (see Directions), decreases the risk of skin cancer and early skin aging caused by the sun

Warnings

For external use only

Do not use

on damaged or broken skin

When using this product

keep out of eyes. Rinse with water to remove.

Stop use and ask a doctor

if rash occurs

Keep out of reach of children.

If swallowed, get medical help or contact a Poison Control Center right away.

Directions

- apply liberally 15 minutes before sun exposure
- reapply:
  • after 80 minutes of swimming or sweating
  • immediately after towel drying
  • at least every 2 hours
- Sun Protection Measures. Spending time in the sun increases your risk of skin cancer and early skin aging. To decrease this risk, regularly use a sunscreen with a Broad Spectrum SPF of 15 or higher and other sun protection measures including:
  • limit time in the sun, especially from 10 a.m. - 2 p.m.
  • wear long-sleeve shirts, pants, hats, and sunglasses
- children under 6 months: Ask a doctor

Inactive Ingredients

Acrylates Copolymer, Acrylates/C10-30 Alkyl Acrylate Crosspolymer, Aloe Barbadensis Leaf Extract, Capryloyl Glycerin/Sebacic Acid Copolymer, Carbomer, Diheptyl Succinate, Diisopropyl Adipate, Disodium EDTA, Ethylhexylglycerin, Glycerin, Hydroxypropyl Methylcellulose, Phenoxyethanol, Propanediol, Sorbitan Oleate, Theobroma Cacao (Cocoa) Seed Butter, Tocopheryl (Vitamin E) Acetate, Triethanolamine, Water

Other Information

- for use on skin only. Avoid contact with fabric
- protect this product from excessive heat and direct sun

Questions or comments?

www.no-ad.com or call toll free 1-800-715-3485

PRINCIPAL DISPLAY PANEL

NO-AD
Sun care
50 Baby
Paraben free
Broadspectrum SPF 50
Sunscreen Lotion
5 FL OZ (148 mL)